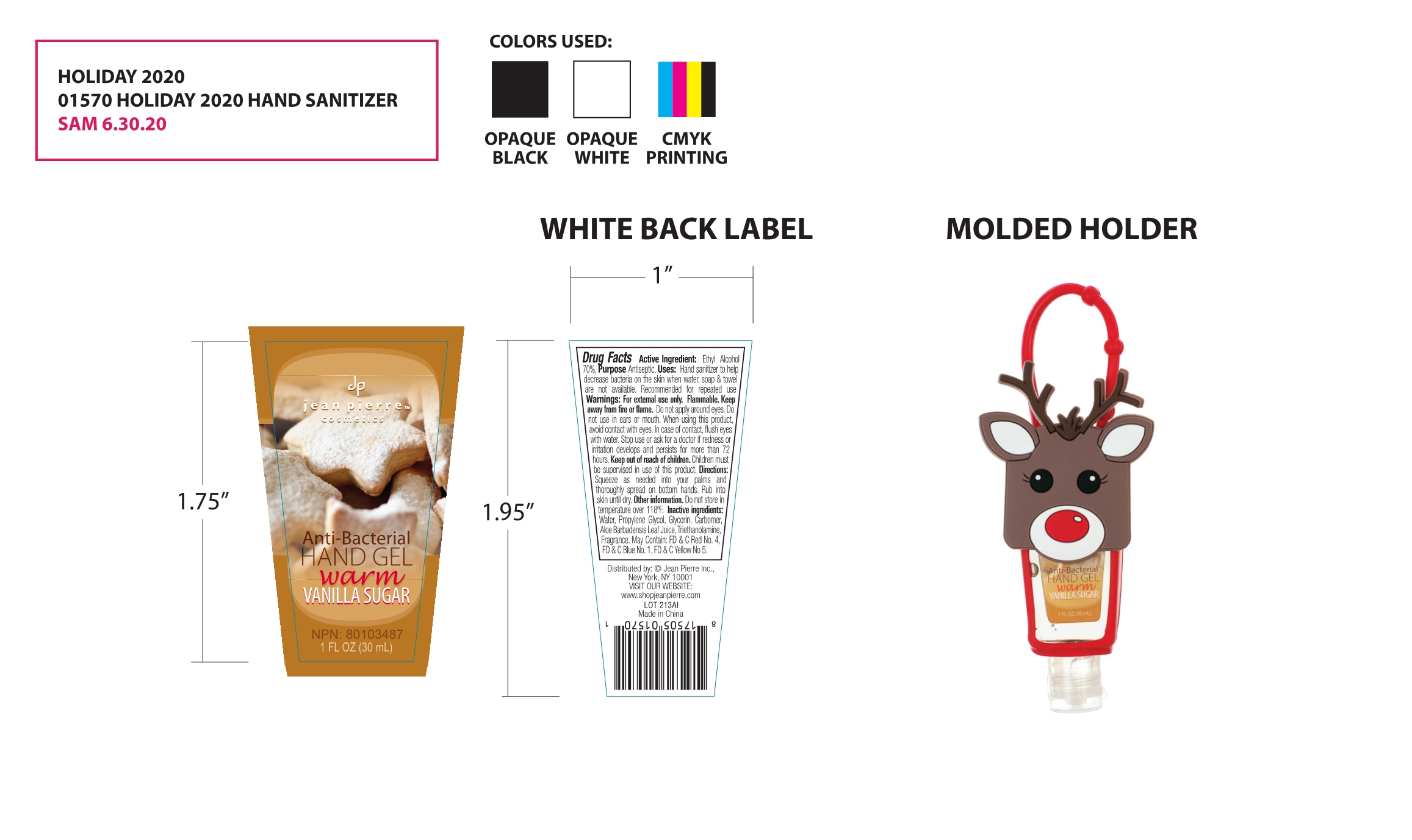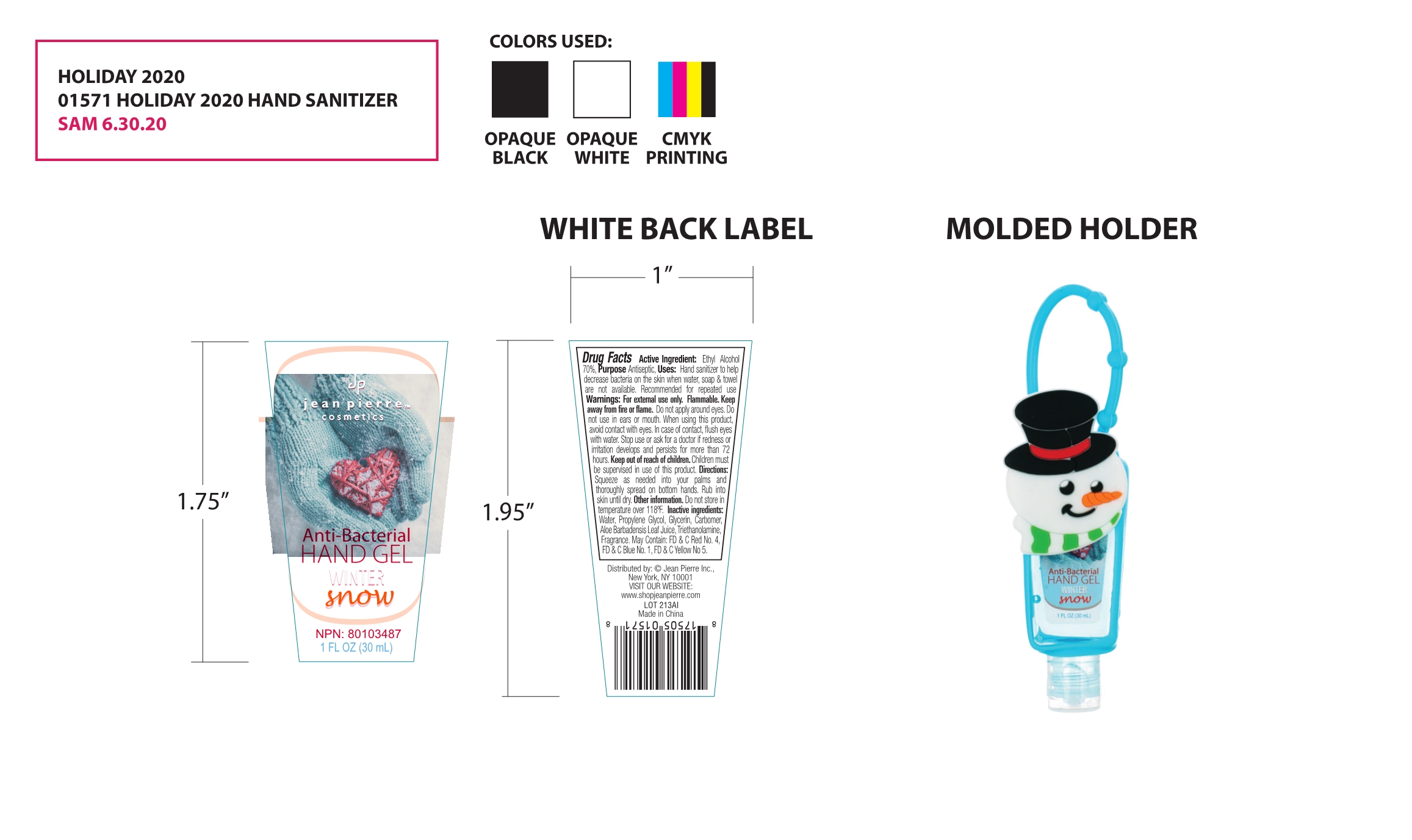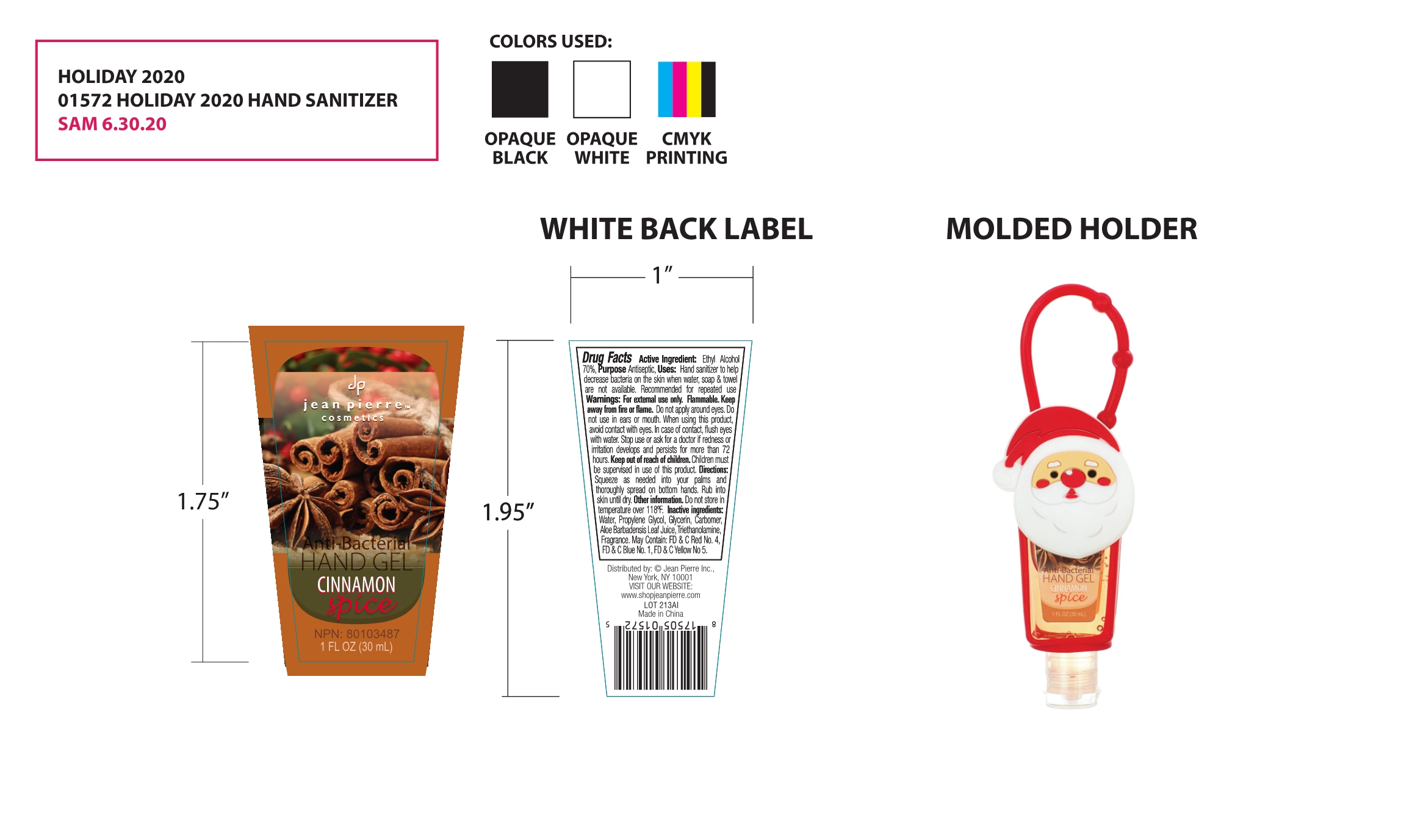 DRUG LABEL: hand gel
NDC: 70483-018 | Form: GEL
Manufacturer: Jean Pierre Inc.
Category: otc | Type: HUMAN OTC DRUG LABEL
Date: 20201016

ACTIVE INGREDIENTS: ALCOHOL 70 mL/100 mL
INACTIVE INGREDIENTS: GLYCERIN; PROPYLENE GLYCOL; WATER; TROLAMINE; FRAGRANCE CLEAN ORC0600327; FD&C RED NO. 40; FD&C BLUE NO. 1; FD&C YELLOW NO. 5; CARBOMER HOMOPOLYMER, UNSPECIFIED TYPE; ALOE VERA LEAF

70483-018
hand gel

Active Ingredient(s)

Ethyl Alcohol 70%

Purpose

Antiseptic

Use

Hand sanitizer to help decrease bacteria on the skin when water, soap & towel are not available. Recommended for repeated use

Do not use

Do not apply around eyes. Do not use in ears or mouth.

When using this product, avoid contact with eyes. In case of contact, flush eyes with water.

Stop use or ask for a doctor if redness or irritation develops and persists for more than 72 hours.

Keep out of reach of children. Children must be supervised in use of this product.

Stop use or ask for a doctor if redness or irritation develops and persists for more than 72 hours.

Keep out of reach of children. Children must be supervised in use of this product.

Directions

Squeeze as needed into your palms and thoroughly spread on bottom hands. Rub into skin until dry.

Other information

Do not store in temperature over 118°F.

Inactive ingredients

Water, Propylene Glycol, Glycerin, Carbomer, Aloe Barbadensis Leaf Juice, Triethanolamine, Fragrance. May Contain: FD & C Red No. 4, FD & C Blue No. 1, FD & C Yellow No 5.